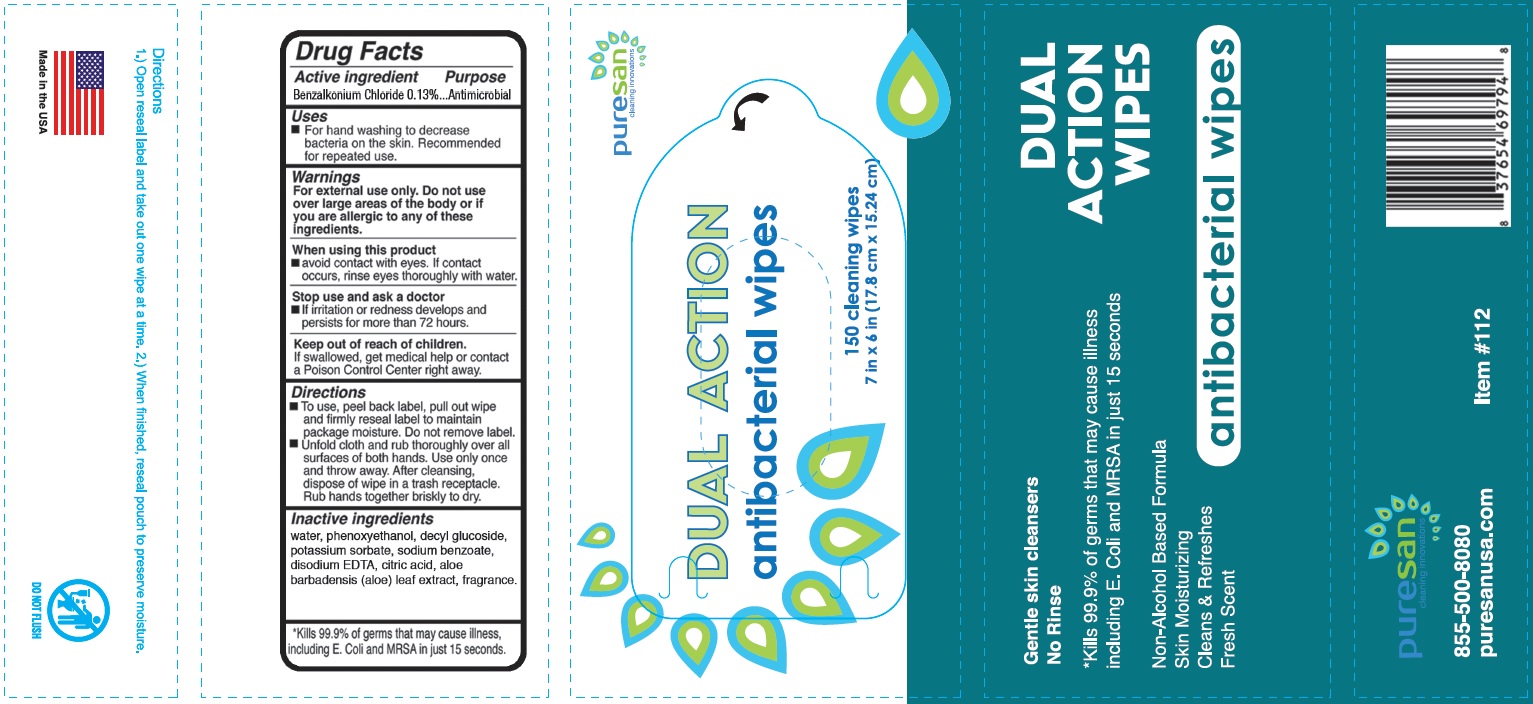 DRUG LABEL: Benzalkonium Chloride
NDC: 73062-401 | Form: CLOTH
Manufacturer: Avro Enterprises LLC
Category: otc | Type: HUMAN OTC DRUG LABEL
Date: 20251205

ACTIVE INGREDIENTS: BENZALKONIUM CHLORIDE 0.13 g/100 1
INACTIVE INGREDIENTS: PHENOXYETHANOL; CITRIC ACID MONOHYDRATE; WATER; DECYL GLUCOSIDE; POTASSIUM SORBATE; EDETATE DISODIUM ANHYDROUS; SODIUM BENZOATE; ALOE VERA LEAF

Dual Action Antibacterial Wipes

Active ingredient

Benzalkonium Chloride 0.13%

Purpose

Antimicrobial

Uses

For had washing to decrease bacteria on the skin. Recommended for repeated use.

Warnings

For external use only. Do not use over large areas of the bosy or if you are allergic to any of these ingredients.

When using this product

avoid contact with eyes. If contact occurs, rinse eyes thoroughly with water.

Stop use and ask a doctor

if irritation or redness develops and persists for more than 72 hours.

Keep out of reach of children

If swallowed, get medical help or contact a Poison Control Center right away.

Directions

- To use, peel back label, pull out wipe and firmly reseal label to maintain package moisture. Do not remove label.
- Unfold cloth and rub thoroughly over all surfaces of both hands. Use only once and throw away. After cleansing, dispose of wipe in a trash receptacle. Rub hands together briskly to dry.

Inactive ingredients

water, phenoxyethanol, decyl glucoside, potassium sorbate, sodium benzoate, disodium EDTA, citric acid, aloe barbadensis (aloe) leaf extract, fragrance.

Principal Display Panel

Dual Action

antibacterial wipes

150 cleaning wipes

7 in x 6 in (17.8 cm x 15.24 cm)

Gentle skin cleansers

No Rinse

*Kills 99.9% of germs that may cause illness including E. Coli and MRSA in just 15 seconds

Non-Alcohol Based Formula

Skin Moisturizing

Cleans & Refreshes

Fresh Scent